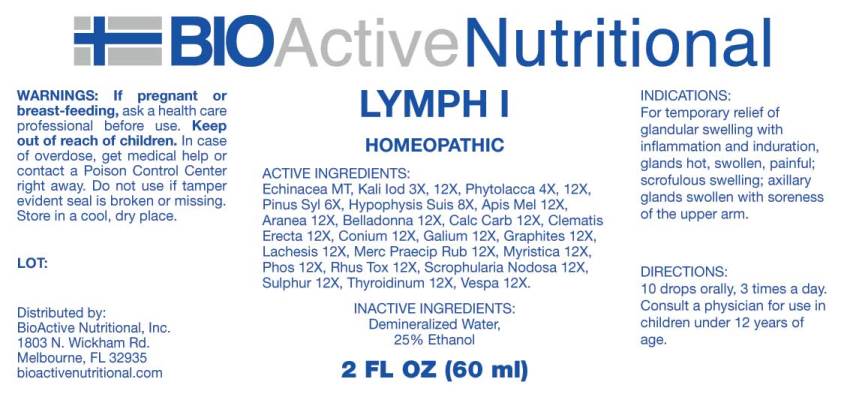 DRUG LABEL: Lymph
NDC: 43857-0477 | Form: LIQUID
Manufacturer: BioActive Nutritional, Inc.
Category: homeopathic | Type: HUMAN OTC DRUG LABEL
Date: 20250516

ACTIVE INGREDIENTS: ECHINACEA ANGUSTIFOLIA 1 [hp_X]/1 mL; POTASSIUM IODIDE 3 [hp_X]/1 mL; PHYTOLACCA AMERICANA ROOT 4 [hp_X]/1 mL; PINUS SYLVESTRIS LEAFY TWIG 6 [hp_X]/1 mL; SUS SCROFA PITUITARY GLAND 8 [hp_X]/1 mL; APIS MELLIFERA 12 [hp_X]/1 mL; ARANEUS DIADEMATUS 12 [hp_X]/1 mL; ATROPA BELLADONNA 12 [hp_X]/1 mL; OYSTER SHELL CALCIUM CARBONATE, CRUDE 12 [hp_X]/1 mL; CLEMATIS RECTA FLOWERING TOP 12 [hp_X]/1 mL; CONIUM MACULATUM FLOWERING TOP 12 [hp_X]/1 mL; GALIUM APARINE 12 [hp_X]/1 mL; GRAPHITE 12 [hp_X]/1 mL; LACHESIS MUTA VENOM 12 [hp_X]/1 mL; MERCURIC OXIDE 12 [hp_X]/1 mL; VIROLA SEBIFERA RESIN 12 [hp_X]/1 mL; PHOSPHORUS 12 [hp_X]/1 mL; TOXICODENDRON PUBESCENS LEAF 12 [hp_X]/1 mL; SCROPHULARIA NODOSA 12 [hp_X]/1 mL; SULFUR 12 [hp_X]/1 mL; SUS SCROFA THYROID 12 [hp_X]/1 mL; VESPA CRABRO 12 [hp_X]/1 mL
INACTIVE INGREDIENTS: WATER; ALCOHOL

Drug Facts:

ACTIVE INGREDIENTS:

Echinacea (Angustifolia) MT, Kali Iodatum 3X, 12X, Phytolacca Decandra 4X, 12X, Pinus Sylvestris 6X, Hypophysis Suis 8X, Apis Mellifica 12X, Aranea Diadema 12X, Belladonna 12X, Calcarea Carbonica 12X, Clematis Erecta 12X, Conium Maculatum 12X, Galium Aparine 12X, Graphites 12X, Lachesis Mutus 12X, Mercurius Praecipitatus Ruber 12X, Myristica Sebifera 12X, Phosphorus 12X, Rhus Tox 12X, Scrophularia Nodosa 12X, Sulphur 12X, Thyroidinum (Suis) 12X, Vespa Crabro 12X.

INDICATIONS:

For temporary relief of glandular swelling with inflammation and induration, glands hot, swollen, painful; scrofulous swelling; axillary glands swollen with soreness of the upper arm.

WARNINGS:

If pregnant or breast-feeding, ask a health care professional before use.

Keep out of reach of children. In case of overdose, get medical help or contact a Poison Control Center right away.

Do not use if tamper evident seal is broken or missing.

Store in cool, dry place.

Keep out of reach of children. In case of overdose, get medical help or contact a Poison Control Center right away.

DIRECTIONS:

10 drops orally, 3 times a day. Consult a physician for use in children under 12 years of age.

INDICATIONS:

For temporary relief of glandular swelling with inflammation and induration, glands hot, swollen, painful; scrofulous swelling; axillary glands swollen with soreness of the upper arm.

INACTIVE INGREDIENTS:

Demineralized Water, 25% Ethanol.

QUESTIONS:

Distributed by:
BioActive Nutritional, Inc.
1803 N. Wickham Rd.
Melbourne, FL 32935
bioactivenutritional.com

PACKAGE LABEL DISPLAY:

BIOActive Nutritional

LYMPH I

HOMEOPATHIC

2 FL OZ (60 ml)